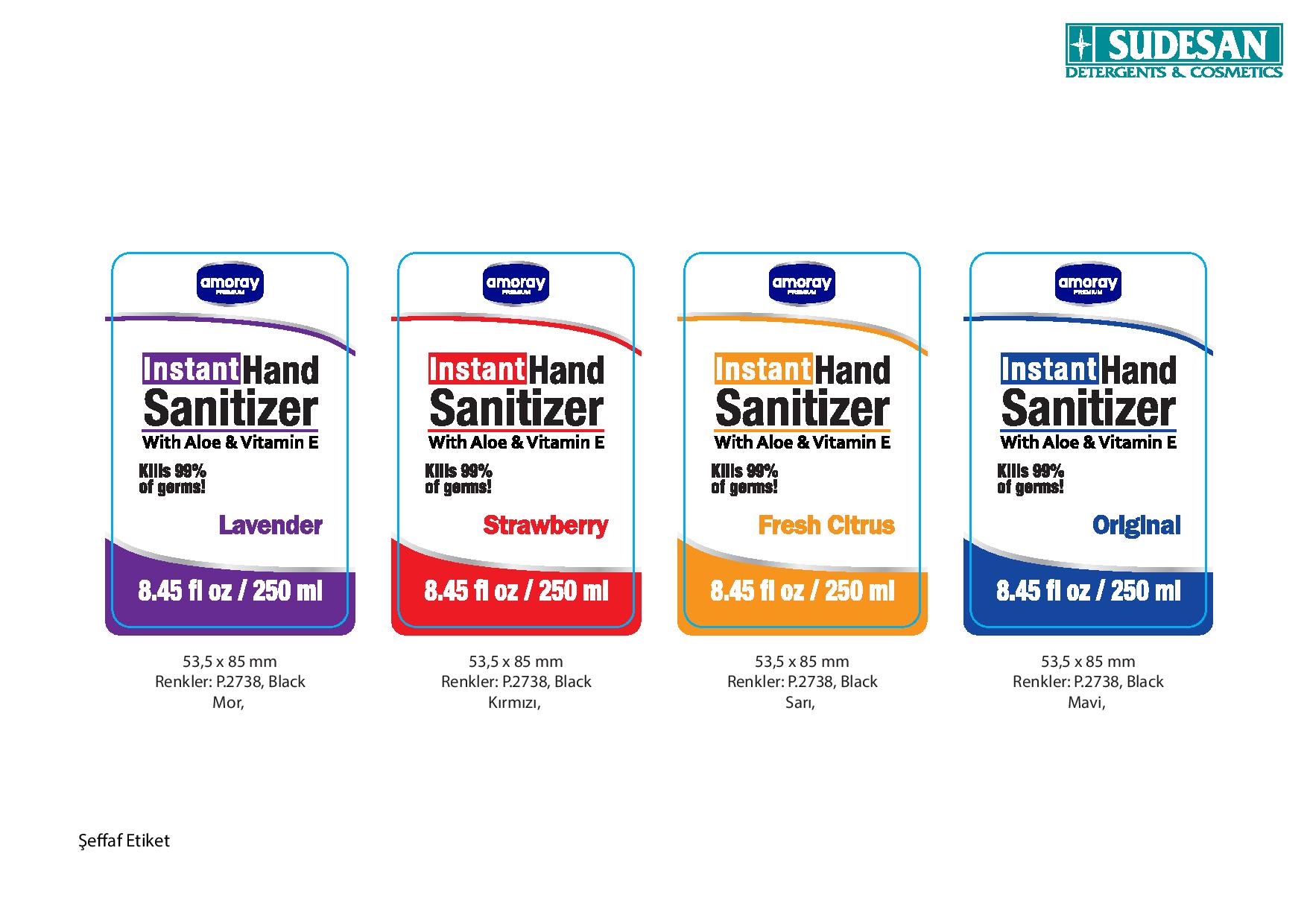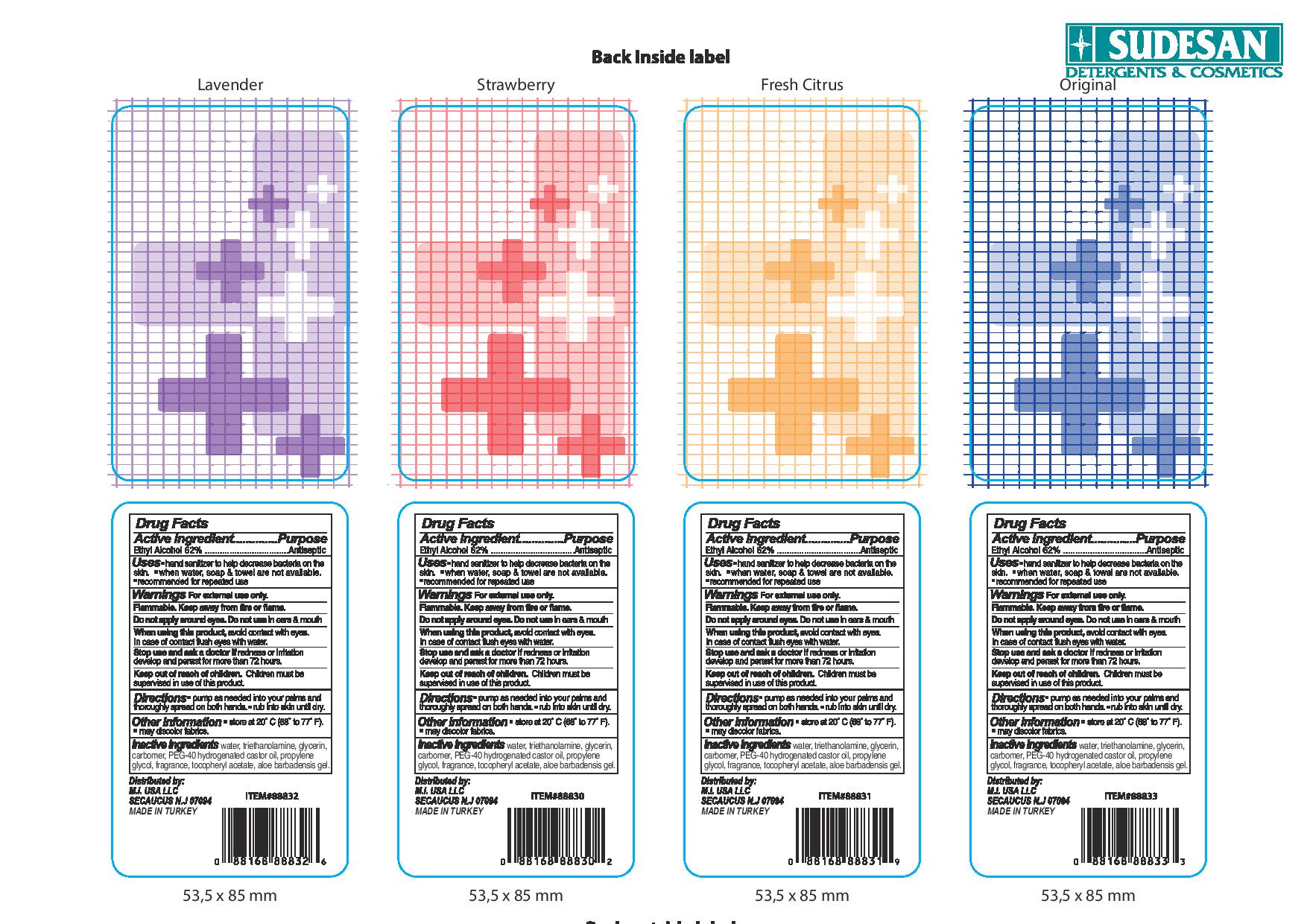 DRUG LABEL: Amoray Premium Instant Hand Sanitizer
NDC: 73580-4220 | Form: LIQUID
Manufacturer: SUDESAN TEMIZLIK URUNLERI VE AMBALAJ SANAYI TICARET ANONIM SIRKETI
Category: otc | Type: HUMAN OTC DRUG LABEL
Date: 20200129

ACTIVE INGREDIENTS: ALCOHOL 250 mL/250 mL
INACTIVE INGREDIENTS: WATER; GLYCERIN; HYDROGENATED CASTOR OIL; PROPYLENE GLYCOL 1,2-DISTEARATE

Instant Hand Sanitizer

ACTIVE INGREDIENT

Ethyl Alcohol 62% ......................... Antiseptic

Keep out of reach of children. Children must be supervised in use of this product

INACTIVE INGREDIENT

Inactive Ingredients water, triethanolamine, glycerin, carbomer, PEG-40 hydrogenated castor oil, propylene gylcol, fragrance, tocopheryl acetate

WARNINGS

For External Use Only:

Flammable. Keep away from fire or flame.

Do not apply around eyes. Do not use in ears or mouth

When using this product, avoid contact with eyes. In cases of contact flush eyes with water

Stop Use and ask doctor if redness or irritation develop and persist for more than 72 hours.

Keep out of reach of children.Children must be supervised in use of this product.

DOSAGE AND ADMINISTRATION

Pump as needed into your palms and thouroughly spreand on both hands - rub into skin until dry.

INDICATIONS AND USAGE

Use Hand Sanitizer to decrease bacteria on the skin. - when water, soap & towel are not available. - Reccomended for repeated use

PURPOSE

hand sanitizer to help decrease bacteria on the skin. - when water, soap & towel are not available. - reccomended for repeated use.